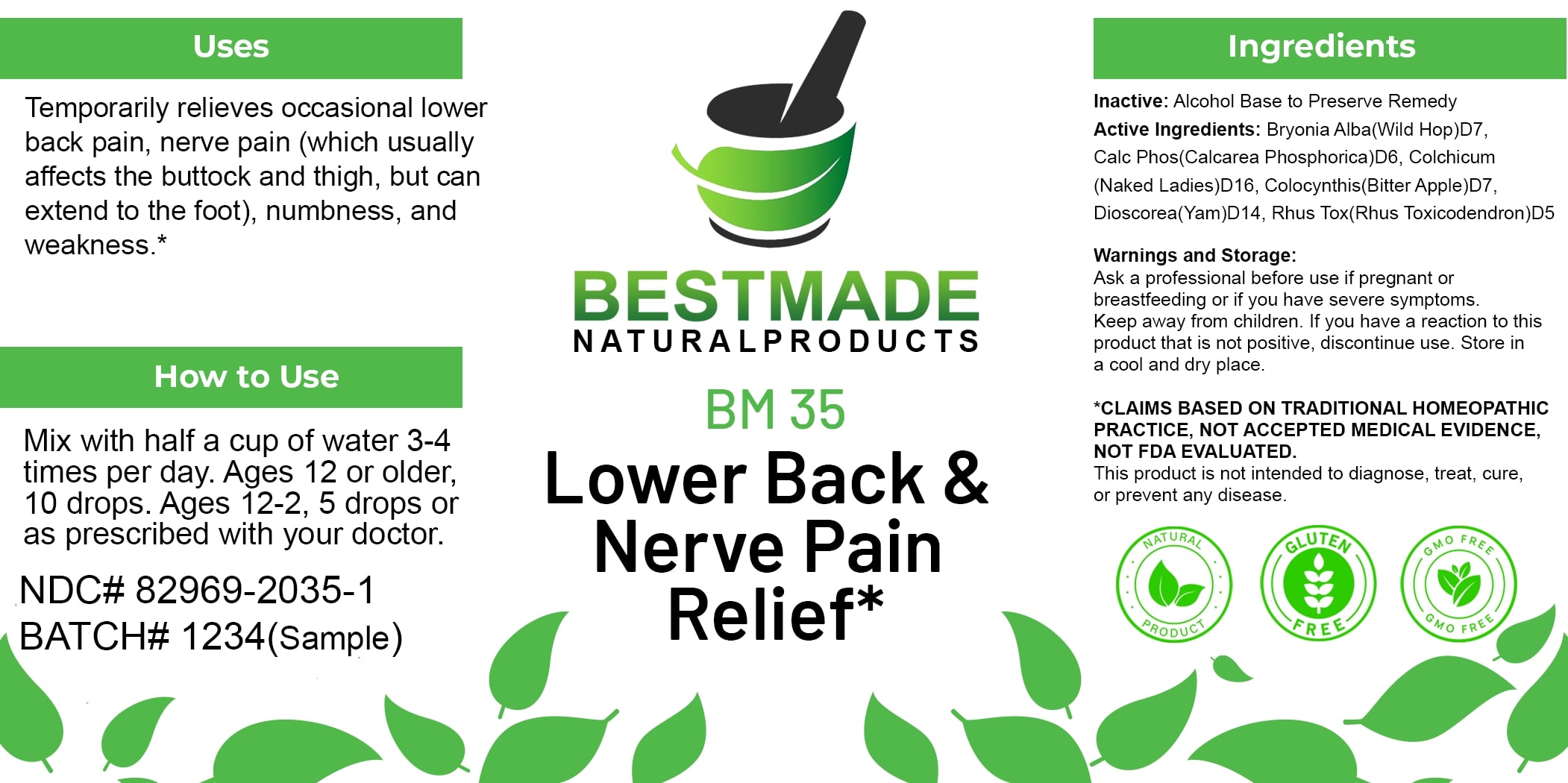 DRUG LABEL: Bestmade Natural Products BM35
NDC: 82969-2035 | Form: LIQUID
Manufacturer: Bestmade Natural Products
Category: homeopathic | Type: HUMAN OTC DRUG LABEL
Date: 20250123

ACTIVE INGREDIENTS: DIOSCOREA VILLOSA TUBER 30 [hp_C]/30 [hp_C]; COLCHICUM AUTUMNALE BULB 30 [hp_C]/30 [hp_C]; CITRULLUS COLOCYNTHIS FRUIT PULP 30 [hp_C]/30 [hp_C]; CALCIUM PHOSPHATE 30 [hp_C]/30 [hp_C]; TOXICODENDRON PUBESCENS LEAF 30 [hp_C]/30 [hp_C]; ATROPA BELLADONNA 30 [hp_C]/30 [hp_C]; BRYONIA ALBA ROOT 30 [hp_C]/30 [hp_C]
INACTIVE INGREDIENTS: ALCOHOL 30 [hp_C]/30 [hp_C]

BM35

DOSAGE AND ADMINISTRATION

How to Use

Mix with half a cup of water 3-4 times per day. Ages 12 or older, 10 drops. Ages 12-2, 5 drops or as prescribed with your doctor.

Uses

Temporarily relieves occasional lower back pain, nerve pain (which usually affects the buttock and thigh, but can extend to the foot), numbness, and weakness.*

*CLAIMS BASED ON TRADITIONAL HOMEOPATHIC PRACTICE, NOT ACCEPTED MEDICAL EVIDENCE, NOT FDA EVALUATED.

This product is not intended to diagnose, treat, cure, or prevent any disease.

Uses

Temporarily relieves occasional lower back pain, nerve pain (which usually affects the buttock and thigh, but can extend to the foot), numbness, and weakness.*

*CLAIMS BASED ON TRADITIONAL HOMEOPATHIC PRACTICE, NOT ACCEPTED MEDICAL EVIDENCE, NOT FDA EVALUATED.

This product is not intended to diagnose, treat, cure, or prevent any disease.

ACTIVE INGREDIENT

Active Ingredients: Bryonia Alba (Wild Hop) D7, Calc Phos (Calcarea Phosphorica) D6, Colchicum (Naked Ladies) D16, Colocynthis (Bitter Apple) D7, Dioscorea (Yam) D14, Rhus Tox (Rhus Toxicodendron) D5

INACTIVE INGREDIENT

Ingredients

Inactive: Alcohol Base to Preserve Remedy

KEEP OUT OF REACH OF CHILDREN

Warnings and Storage:

Ask a professional before use if pregnant or breastfeeding or if you have severe symptoms. Keep away from children. If you have a reaction to this product that is not positive, discontinue use. Store in a cool and dry place.

Warnings and Storage:

Ask a professional before use if pregnant or breastfeeding or if you have severe symptoms. Keep away from children. If you have a reaction to this product that is not positive, discontinue use. Store in a cool and dry place.

*CLAIMS BASED ON TRADITIONAL HOMEOPATHIC PRACTICE, NOT ACCEPTED MEDICAL EVIDENCE, NOT FDA EVALUATED.

This product is not intended to diagnose, treat, cure, or prevent any disease.

Entire package label